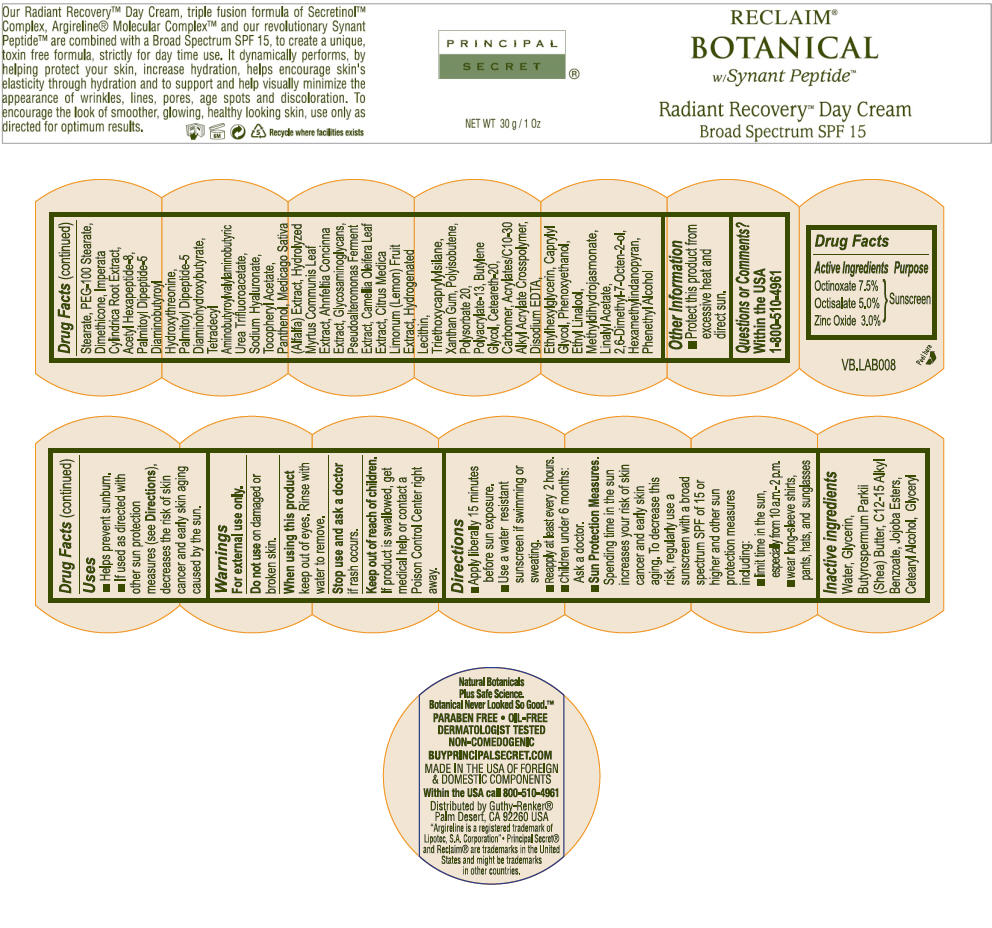 DRUG LABEL: Principal Secret Reclaim Botanical (with SP) Radiant Recovery Day Broad Spectrum  SPF 15
NDC: 70605-029 | Form: CREAM
Manufacturer: Guthy-Renker LLC
Category: otc | Type: HUMAN OTC DRUG LABEL
Date: 20240111

ACTIVE INGREDIENTS: Octinoxate 7.5 g/100 g; Octisalate 5 g/100 g; Zinc Oxide 3 g/100 g
INACTIVE INGREDIENTS: Water; Glycerin; SHEA BUTTER; Alkyl (C12-15) Benzoate; JOJOBA OIL; CETOSTEARYL ALCOHOL; GLYCERYL MONOSTEARATE; PEG-100 Stearate; Imperata Cylindrica Root; Dimethicone; Acetyl Hexapeptide-8; PALMITOYLLYSYLVALYLDIAMINOBUTYROYLTHREONINE; PALMITOYLLYSYLVALYLDIAMINOBUTYRIC ACID; HYALURONATE SODIUM; .ALPHA.-TOCOPHEROL ACETATE; Panthenol; MEDICAGO SATIVA WHOLE; AHNFELTIOPSIS CONCINNA; CAMELLIA OLEIFERA LEAF; LEMON; Triethoxycaprylylsilane; Xanthan Gum; POLYISOBUTYLENE (1000 MW); Polysorbate 20; Butylene Glycol; POLYOXYL 20 CETOSTEARYL ETHER; CARBOMER INTERPOLYMER TYPE A (ALLYL SUCROSE CROSSLINKED); EDETATE DISODIUM; Ethylhexylglycerin; Caprylyl Glycol; Phenoxyethanol; Ethyl Linalool; Methyl Dihydrojasmonate (Synthetic); Linalyl Acetate; DIHYDROMYRCENOL; Hexamethylindanopyran; Phenylethyl Alcohol

Principal Secret® Reclaim® Botanical (with SP) Radiant Recovery™ Day Cream Broad Spectrum SPF 15

Drug Facts

Active ingredients

Octinoxate 7.5%
Octisalate 5%
Zinc Oxide 3.0%

Purpose

Sunscreen

Uses

- helps prevent sunburn
- if used as directed with other sun protection measures (see Directions), decreases the risk of skin cancer and early skin aging caused by the sun

Warnings

Skin Cancer/Skin Aging Alert

Spending time in the sun increases your risk of skin cancer and early skin aging. This product has been shown only to prevent sunburn, not skin cancer or early skin aging.

For external use only

Do not use

on damaged or broken skin.

When using this product

keep out of eyes. Rinse with water to remove.

Stop use and ask a doctor

if rash occurs.

Keep out of reach of children.

If product is swallowed, get medical help or contact a Poison Control Center right away.

Directions

- apply liberally 15 minutes before sun exposure
- use a water resistant sunscreen if swimming or sweating
- reapply at least every 2 hours
- children under 6 months: Ask a doctor

Inactive ingredients

Water, Glycerin, Butyrospermum Parkii (Shea) Butter, C12-15 Alkyl Benzoate, Jojoba Esters, Cetearyl Alcohol, Glyceryl Stearate, PEG-100 Stearate, Dimethicone, Imperata Cylindrica Root Extract, Acetyl Hexapeptide-8, Palmitoyl Dipeptide-5 Diaminobutyroyl Hydroxythreonine, Palmitoyl Dipeptide-5 Diaminohydroxybutyrate, Tetradecyl Aminobutyroylvalylaminobutyric Urea Trifluoroacetate, Sodium Hyaluronate, Tocopheryl Acetate, Panthenol, Medicago Sativa (Alfalfa) Extract, Hydrolyzed Myrtus Communis Leaf Extract, Ahnfeltia Concinna Extract, Glycosaminoglycans, Pseudoalteromonas Ferment Extract, Camellia Oleifera Leaf Extract, Citrus Medica Limonum (Lemon) Fruit Extract, Hydrogenated Lecithin, Triethoxycaprylylsilane, Xanthan Gum, Polyisobutene, Polysorbate 20, Polyacrylate-13, Butylene Glycol, Ceteareth-20, Carbomer, Acrylates/C10-30 Alkyl Acrylate Crosspolymer, Disodium EDTA, Ethylhexylglycerin, Caprylyl Glycol, Phenoxyethanol, Ethyl Linalool, Methyldihydrojasmonate, Linalyl Acetate, 2,6-Dimethyl-7-Octen-2-ol, Hexamethylindanopyran, Phenethyl Alcohol.

Other information

- protect this product from excessive heat and direct sun

Questions or comments?

Within US 1-800-510-4961

Distributed by Guthy-Renker®
Palm Desert, CA 92260 USA

PRINCIPAL DISPLAY PANEL - 30 g Jar Label

RECLAIM®
BOTANICAL
w/Synant Peptide™

Radiant Recovery™ Day Cream
Broad Spectrum SPF 15